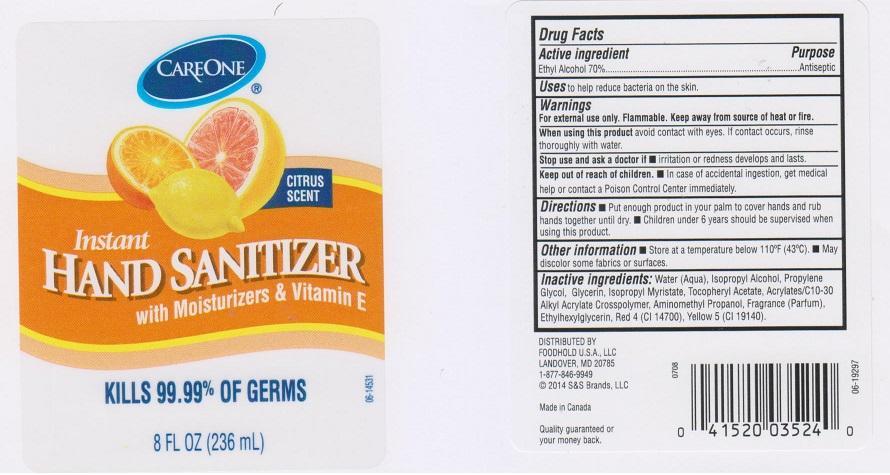 DRUG LABEL: CARE ONE
NDC: 41520-042 | Form: LIQUID
Manufacturer: AMERICAN SALES COMPANY
Category: otc | Type: HUMAN OTC DRUG LABEL
Date: 20150529

ACTIVE INGREDIENTS: ALCOHOL 700 mg/1 mL
INACTIVE INGREDIENTS: WATER; ISOPROPYL ALCOHOL; PROPYLENE GLYCOL; GLYCERIN; ISOPROPYL MYRISTATE; .ALPHA.-TOCOPHEROL ACETATE; CARBOMER COPOLYMER TYPE A (ALLYL PENTAERYTHRITOL CROSSLINKED); METHACRYLIC ACID - METHYL METHACRYLATE COPOLYMER (1:1); AMINOMETHYLPROPANOL; ETHYLHEXYLGLYCERIN; FD&C RED NO. 4; FD&C YELLOW NO. 5

ACTIVE INGREDIENT

ETHYL ALCOHOL 70%

PURPOSE

ANTISEPTIC

USES

TO HELP REDUCE BACTERIA ON THE SKIN

WARNINGS

FOR EXTERNAL USE ONLY. FLAMMABLE. KEEP AWAY FROM SOURCE OF HEAT OR FIRE

WHEN USING THIS PRODUCT

AVOID CONTACT WITH EYES. IF CONTACT OCCURS, RINSE THOROUGHLY WITH WATER

STOP USE AND ASK A DOCTOR IF

IRRITATION OR REDNESS DEVELOPS AND LASTS

KEEP OUT OF REACH OF CHILDREN

IN CASE OF ACCIDENTAL INGESTION, GET MEDICAL HELP OR CONTACT A POISON CONTROL CENTER IMMEDIATELY.

DIRECTIONS

- PUT ENOUGH PRODUCT IN YOUR PALM TO COVER HANDS AND RUB HANDS TOGETHER UNTIL DRY
- CHILDREN UNDER 6 YEARS SHOULD BE SUPERVISED WHEN USING THIS PRODUCT

OTHER INFORMATION

- STORE AT A TEMPERATURE BELOW 110°F (43ºC)
- MAY DISCOLOR SOME FABRICS OR SURFACES

INACTIVE INGREDIENTS

WATER (AQUA), ISOPROPYL ALCOHOL, PROPYLENE GLYCOL, GLYCERIN, ISOPROPYL MYRISTATE, TOCOPHERYL ACETATE, ACRYLATES/C10-30 ALKYL ACRYLATE CROSSPOLYMER, AMINOMETHYL PROPANOL, FRAGRANCE (PARFUM), ETHYLHEXYLGLYCERIN, RED 4 (CI 14700), YELLOW 5 (ci 19140)